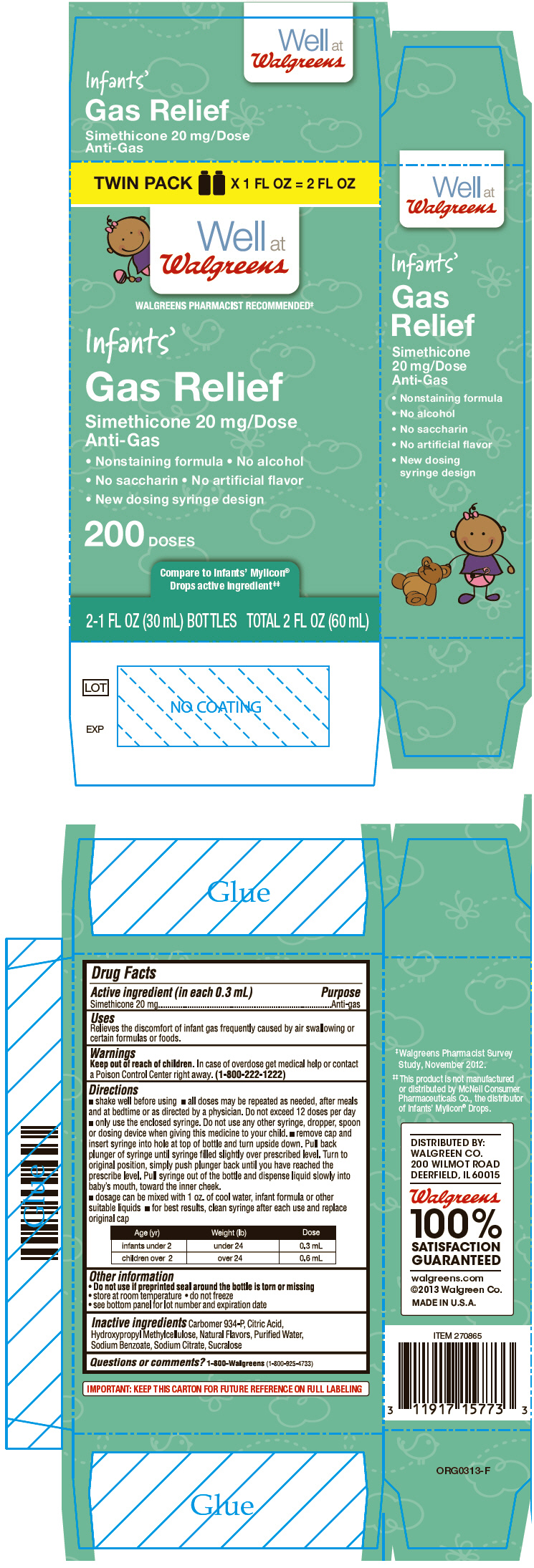 DRUG LABEL: Infants Gas Relief 
NDC: 0363-5773 | Form: LIQUID
Manufacturer: Walgreens
Category: otc | Type: HUMAN OTC DRUG LABEL
Date: 20131203

ACTIVE INGREDIENTS: DIMETHICONE 20 mg/0.3 mL
INACTIVE INGREDIENTS: SODIUM BENZOATE; CITRIC ACID MONOHYDRATE; HYPROMELLOSES; CARBOMER HOMOPOLYMER TYPE B (ALLYL SUCROSE CROSSLINKED); SUCRALOSE; VANILLIN; SODIUM CITRATE; WATER

Infant's Gas Relief
Non-Staining Formula

Drug Facts

Active ingredient (in each 0.3 mL)

Simethicone 20 mg

Purpose

Anti-gas

Uses

Relieves the discomfort of infant gas frequently caused by air swallowing or certain formulas or foods.

Warnings

Keep out of reach of children. In case of overdose get medical help or contact a Poison Control Center right away. (1-800-222-1222)

Directions

- shake well before using
- all doses may be repeated as needed, after meals and at bedtime or as directed by a physician. Do not exceed 12 doses per day
- only use the enclosed syringe. Do not use any other syringe, dropper, spoon or dosing device when giving this medicine to your child.
- remove cap and insert syringe into hole at top of bottle and turn upside down. Pull back plunger of syringe until syringe filled slightly over prescribed level. Turn to original position, simply push plunger back until you have reached the prescribe level. Pull syringe out of the bottle and dispense liquid slowly into baby's mouth, toward the inner cheek.
- dosage can be mixed with 1 oz. of cool water, infant formula or other suitable liquids
- for best results, clean syringe after each use and replace original cap

Age (yr) | Weight (lb) | Dose
infants under 2 | under 24 | 0.3 mL
children over 2 | over 24 | 0.6 mL

Other information

- Do not use if preprinted seal around the bottle is torn or missing
- store at room temperature
- do not freeze
- see bottom panel for lot number and expiration date

Inactive ingredients

Carbomer 934-P, Citric Acid, Hydroxypropyl Methylcellulose, Natural Flavors, Purified Water, Sodium Benzoate, Sodium Citrate, Sucralose

Questions or comments?

1-800-Walgreens (1-800-925-4733)

DISTRIBUTED BY:
WALGREEN CO.
200 WILMOT ROAD
DEERFIELD, IL 60015

PRINCIPAL DISPLAY PANEL - 2-Bottle Carton

TWIN PACK X 1 FL OZ = 2 FL OZ

Well at
Walgreens

WALGREENS PHARMACIST RECOMMENDED‡

Infants'

Gas Relief

Simethicone 20 mg/Dose
Anti-Gas

• Nonstaining formula • No alcohol

• No saccharin • No artificial flavor

• New dosing syringe design

200 DOSES

Compare to Infants' Mylicon®
Drops active ingredient‡‡

2-1 FL OZ (30 mL) BOTTLES TOTAL 2 FL OZ (60 mL)